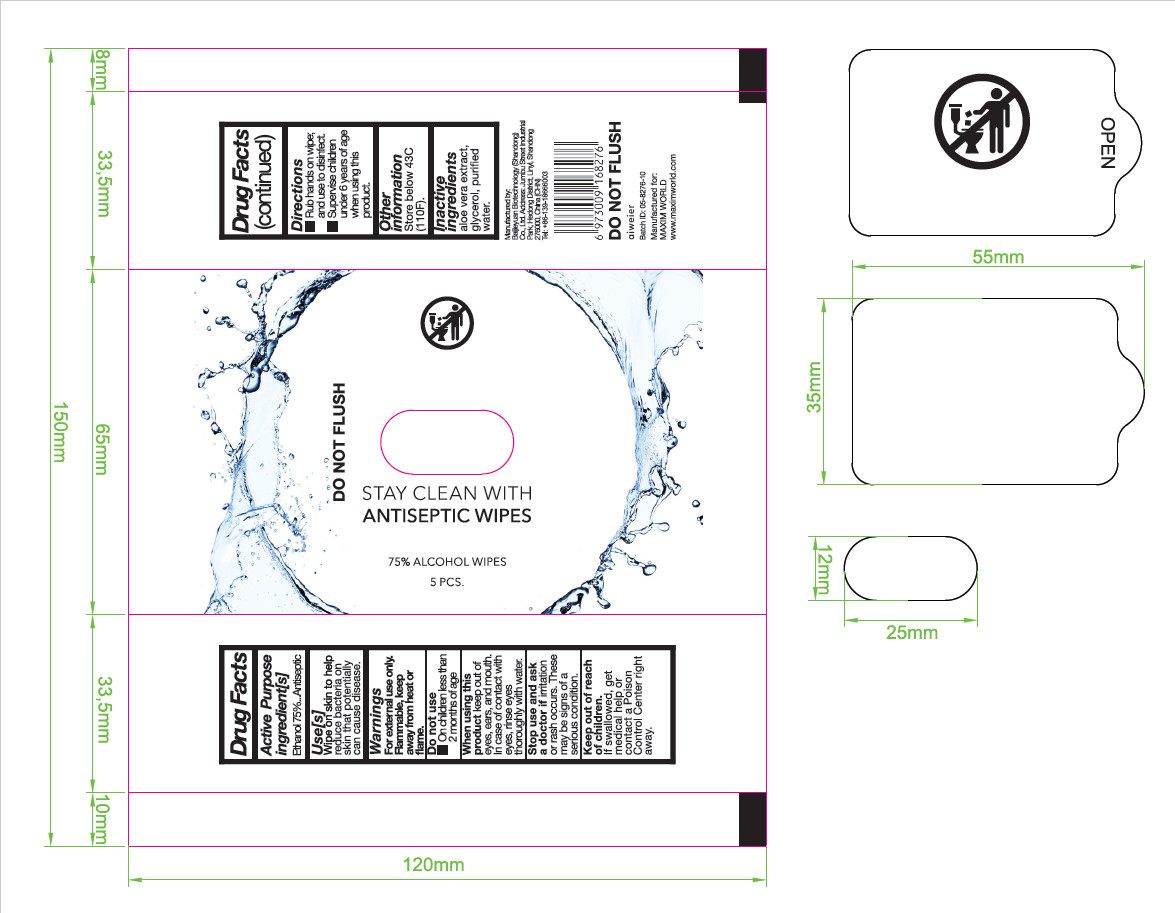 DRUG LABEL: 75% Alcohol Wipes
NDC: 55490-036 | Form: CLOTH
Manufacturer: Baijieyuan Biotechnology (Shandong) Co., Ltd.
Category: otc | Type: HUMAN OTC DRUG LABEL
Date: 20230414

ACTIVE INGREDIENTS: ALCOHOL 75 mL/100 1
INACTIVE INGREDIENTS: ALOE; GLYCERIN; WATER

DOSAGE AND ADMINISTRATION

Store below 110°F (43°C)

INACTIVE INGREDIENT

Glycerol

Aloe extract

Pure water

INDICATIONS AND USAGE

Rub hands on wipes and use to disfect

ACTIVE INGREDIENT

Ethyl alcohol

keep out of reach of children

PURPOSE

Disinfection
Sterilization
No Rinseing

WARNINGS

For external use only,Keep away from heat or flame.